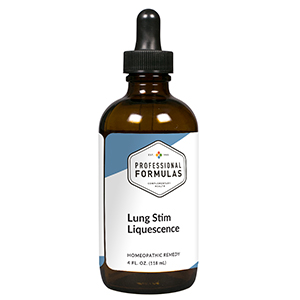 DRUG LABEL: Lung Stim Liquescence
NDC: 63083-3026 | Form: LIQUID
Manufacturer: Professional Complementary Health Formulas
Category: homeopathic | Type: HUMAN OTC DRUG LABEL
Date: 20190815

ACTIVE INGREDIENTS: EUCALYPTUS GLOBULUS LEAF 2 [hp_X]/118 mL; BRYONIA ALBA ROOT 3 [hp_X]/118 mL; EPINEPHRINE 6 [hp_X]/118 mL; DROSERA ROTUNDIFOLIA WHOLE 6 [hp_X]/118 mL; IPECAC 6 [hp_X]/118 mL; POTASSIUM DICHROMATE 6 [hp_X]/118 mL; BEEF LUNG 6 [hp_X]/118 mL; SANGUINARIA CANADENSIS ROOT 6 [hp_X]/118 mL; AMARYLLIS BELLADONNA WHOLE 12 [hp_X]/118 mL
INACTIVE INGREDIENTS: ALCOHOL; WATER

T26

ACTIVE INGREDIENTS

Eucalyptus globulus 2X
Bryonia 3X
Adrenalinum 6X
Drosera rotundifolia 6X
Ipecacuanha 6X
Kali bichromicum 6X
Lung 6X
Sanguinaria canadensis 6X
Belladonna 12X

QUESTIONS

Professional Formulas

PO Box 2034 Lake Oswego, OR 97035

INDICATIONS

For the temporary relief of shortness of breath, wheezing, cough, mild chest pain, or fatigue.*

PURPOSE

*Claims based on traditional homeopathic practice, not accepted medical evidence. Not FDA evaluated.

WARNINGS

Severe or persistent symptoms may be serious. Consult a doctor promptly. Keep out of the reach of children. In case of overdose, get medical help or contact a poison control center right away. If pregnant or breastfeeding, ask a healthcare professional before use.

Keep out of the reach of children.

PREGNANCY OR BREAST FEEDING

If pregnant or breastfeeding, ask a healthcare professional before use.

DIRECTIONS

Place drops under tongue 30 minutes before/after meals. Adults and children 12 years and over: Take one full dropper up to 2 times per day. Consult a physician for use in children under 12 years of age.

OTHER INFORMATION

Tamper resistant. If seal is broken, do not use. After opening, close container tightly and store at room temperature away from heat.

INACTIVE INGREDIENTS

20% ethanol, purified water.

LABEL

Est 1985

Professional Formulas

Complementary Health

Lung Stim Liquescence

Homeopathic Remedy

4 FL. OZ. (118 mL)